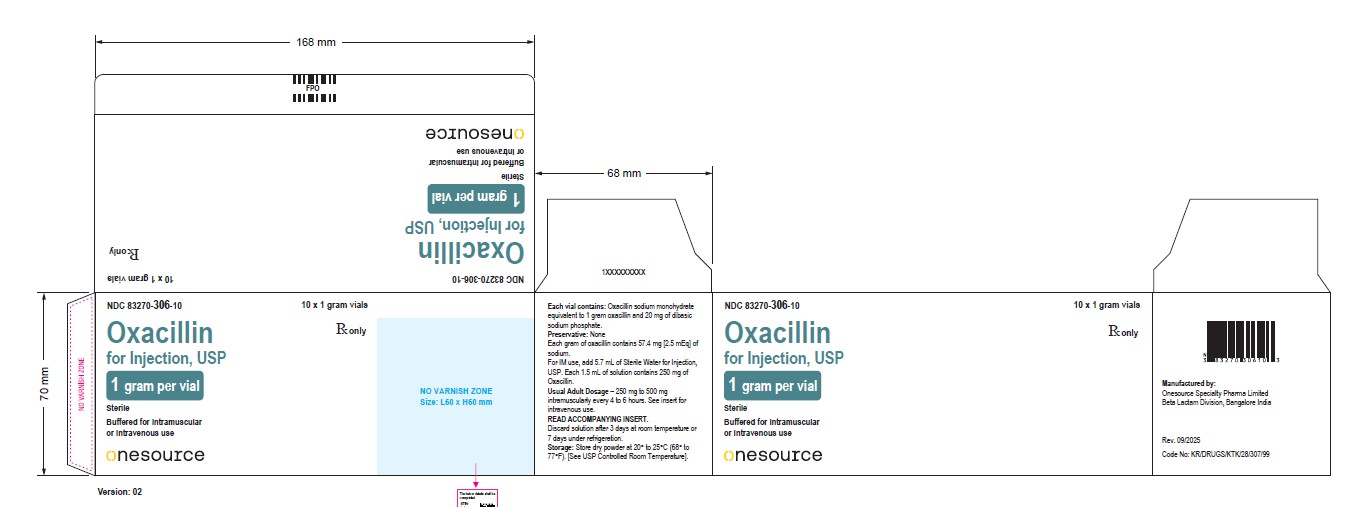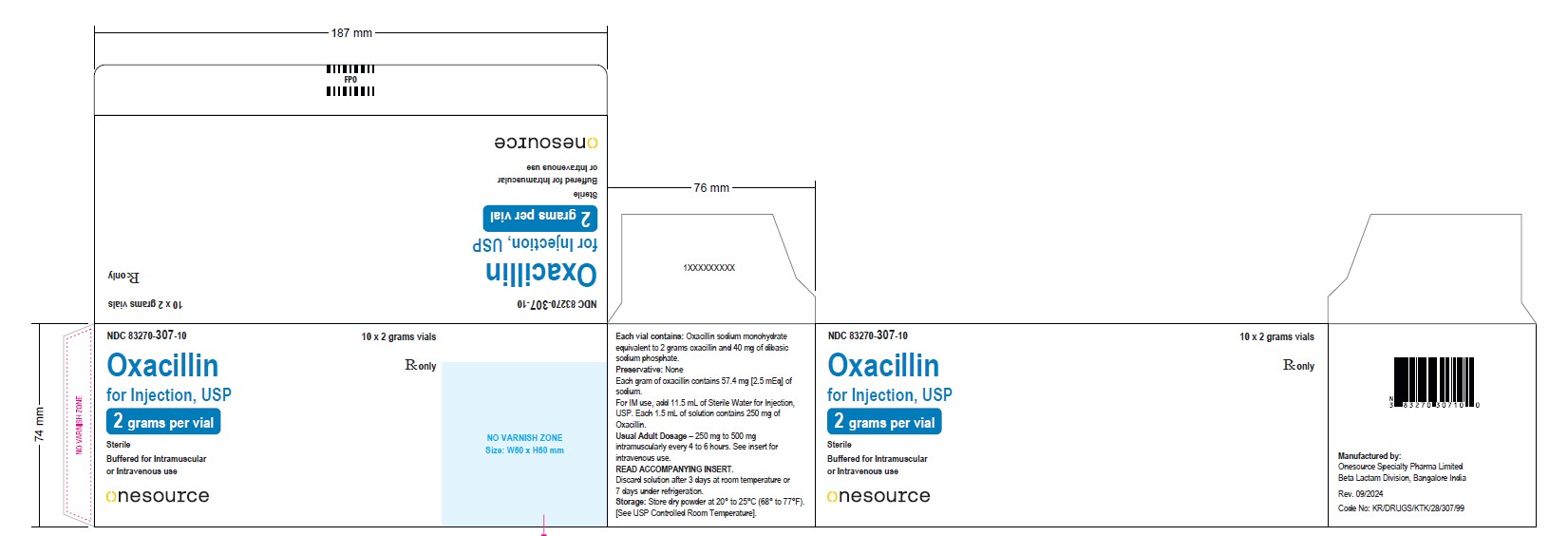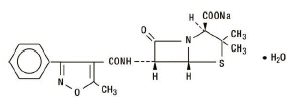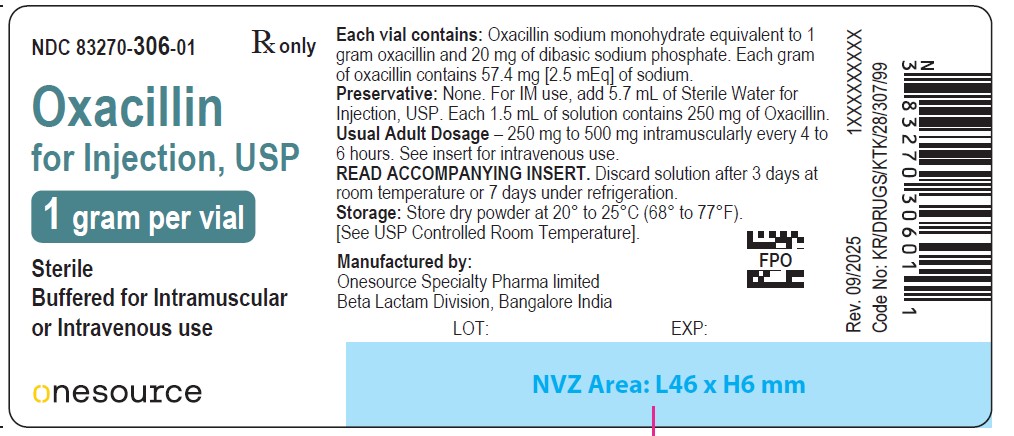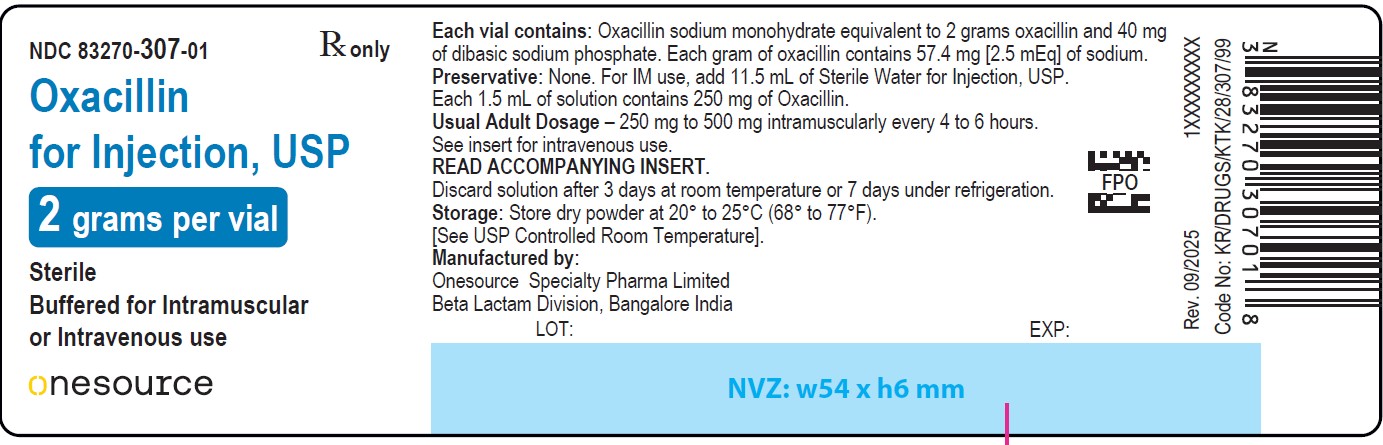 DRUG LABEL: oxacillin
NDC: 83270-306 | Form: INJECTION, POWDER, FOR SOLUTION
Manufacturer: Onesource Specialty Pharma Limited
Category: prescription | Type: HUMAN PRESCRIPTION DRUG LABEL
Date: 20251231

ACTIVE INGREDIENTS: OXACILLIN SODIUM 1 g/1 1
INACTIVE INGREDIENTS: SODIUM PHOSPHATE, DIBASIC

Oxacillin for Injection, USP

For Intramuscular or Intravenous Injection

Rx only

To reduce the development of drug-resistant bacteria and maintain the effectiveness of oxacillin for injection and other antibacterial drugs, oxacillin for injection should be used only to treat or prevent infections that are proven or strongly suspected to be caused by bacteria.

DESCRIPTION

Oxacillin for Injection, USP is a semisynthetic penicillin antibiotic derived from the penicillin nucleus, 6-amino-penicillanic acid. It is resistant to inactivation by the enzyme penicillinase (beta-lactamase). It is the sodium salt in parenteral dosage form for intramuscular or intravenous use. Each vial of oxacillin for injection, USP contains oxacillin sodium monohydrate equivalent to 1 gram or 2 grams of oxacillin. The sodium content is 57.4 mg (2.5 mEq) per gram oxacillin. The product is buffered with 20 mg dibasic sodium phosphate per gram oxacillin. Oxacillin for injection, USP is white to off white powder and gives a clear solution upon reconstitution. OXACILLIN SODIUM The chemical name of oxacillin sodium is 4-Thia-1-azabicyclo[3.2.0]heptane-2-carboxylic acid, 3,3-dimethyl-6-[[(5-methyl-3-phenyl-4-isoxazolyl)carbonyl]-amino]-7-oxo-, monosodium salt, monohydrate, [2S-(2α,5α,6ß)]-. It is resistant to inactivation by the enzyme penicillinase (beta-lactamase). The molecular formula of oxacillin sodium is C19H18N3NaO5S•H2O. The molecular weight is 441.43.

CLINICAL PHARMACOLOGY

Intravenous administration provides peak serum levels approximately 5 minutes after the injection is completed. Slow I.V administration of 500 mg gives a peak serum level of 43 mcg/mL after 5 minutes with a half-life of 20 to 30 minutes.

Oxacillin sodium, with normal doses, has insignificant concentrations in the cerebrospinal and ascitic fluids. It is found in therapeutic concentrations in the pleural, bile, and amniotic fluids.

Oxacillin Sodium is rapidly excreted as unchanged drug in the urine by glomerular filtration and active tubular secretion. The elimination half-life for oxacillin is about 0.5 hours. Nonrenal elimination includes hepatic inactivation and excretion in bile.

Oxacillin sodium binds to serum protein, mainly albumin. The degree of protein binding reported varies with the method of study and the investigator, but generally has been found to be 94.2 ± 2.1%.

Probenecid blocks the renal tubular secretion of penicillins. Therefore, the concurrent administration of probenecid prolongs the elimination of oxacillin and, consequently, increases the serum concentration.

Intramuscular injections give peak serum levels 30 minutes after injection. A 250 mg dose gives a level of 5.3 mcg/mL while a 500 mg dose peaks at 10.9 mcg/mL. Intravenous injection gives a peak about 5 minutes after the injection is completed. Slow IV dosing with 500 mg gives a 5 minute peak of 43 mcg/mL with a half-life of 20 to 30 minutes.

MICROBIOLOGY

Mode of Action

Penicillinase-resistant penicillins exert a bactericidal action against penicillin susceptible microorganisms during the state of active multiplication. All penicillins inhibit the biosynthesis of the bacterial cell wall.

Mechanism of Resistance

Resistance to penicillins may be mediated by destruction of the beta-lactam ring by a beta-lactamase, altered affinity of penicillin for target, or decreased penetration of the antibiotic to reach the target site.

Cross Resistance

Resistance to oxacillin (or cefoxitin) implies resistance to all other beta-lactam agents, except newer agents with activity against methicillin-resistant Staphylococcus aureus.

Susceptibility Test Methods

When available, the clinical microbiology laboratory should provide of in vitro susceptibility test results for antimicrobial drugs used in local hospitals and practice areas to the physician as periodic reports that describe the susceptibility profile of nosocomial and community-acquired pathogens. These reports should aid the physician in selecting the most effective antibacterial drug for treatment.

Dilution techniques

Quantitative methods are used to determine antimicrobial minimum inhibitory concentrations (MICs). These MICs provide estimates of the susceptibility of bacteria to antimicrobial compounds. The MICs should be determined using a standardized test method^1,2(broth and/or agar). The MIC values should be interpreted according to the criteria in Table 1.

Diffusion techniques

Quantitative methods that require measurement of zone diameters can also provide reproducible estimates of the susceptibility of bacteria to antimicrobial compounds. The zone size should be determined using a standardized method.^2,3.It has been determined that the most accurate method to test the susceptibility of microorganisms to penicillinase resistant penicillins, including oxacillin, by disk diffusion is achieved using disks impregnated with 30 mcg cefoxitin. Interpretation involves correlation of the diameter obtained with the cefoxitin disk test with the MIC for oxacillin^2. Reports from the laboratory providing results of the standard single-disk susceptibility test with a 30 microgram cefoxitin disk should be interpreted according to the following criteria in Table 1.

Table 1: Susceptibility Test Interpretive Criteria for Oxacillin

Pathogen | Antimicrobial | Disk | Disk Diffusion Zone Diameter |  |  | Minimum Inhibitory
 | Agent | Content | (mm)a |  |  | Concentrations (mcg/mL)
 |  |  | S | I | R | S | I | R
Staphylococcus aureus and S. lugdenensisC | Oxacillin | - | - | - | - | ≤ 2; (oxacillin) | - | ≥ 4; (oxacillin)
 |  | 30 mcg; cefoxitinb | ≥ 22 | - | ≤ 21 | ≤ 4; (cefoxitin) | - | ≥ 8; (cefoxitin)
Coagulase- negative Staphylococci except S.lugdenensis | Oxacillind | - | - | - | - | ≤ 0.25 | - | ≥ 0.5
 |  | 30 mcg; cefoxitinb | ≥25 | - | ≤24 | - | - | -

S=susceptible, I=intermediate, R-resistant

aIn most staphylococcal isolates, oxacillin resistance is mediated by mecA, encoding the penicillin binding protein 2a (PBP2a, also called PBP2’). Isolates that test positive for mecA or PBP2a should be reported as oxacillin resistant.”

2bCefoxitin is used as a surrogate for oxacillin; report oxacillin susceptible or resistant based on the cefoxitin result.

2cIf both cefoxitin and oxacillin are tested against S. aureusor S. lugdenensis, and either result is resistant, the organism should be reported as oxacillin resistant.

2dOxacillin MIC interpretive criteria may overcall resistance for some coagulase-negative staphylococci (CoNS), because some non- S. epidermidisstrains for which the oxacillin MICs are 0.5 to 2 mcg/ml lack mecA. For serious infections with CoNS other than S. epidermidis, testing for mecAor for PBP 2a or with cefoxitin disk diffusion

A report of “Susceptible” indicates that the antimicrobial is likely to inhibit the growth of the pathogen if the antimicrobial compound reaches the concentrations at the infection site necessary to inhibit growth of the pathogen. A report of “Intermediate” indicates that the result should be considered equivocal, and if the microorganism is not fully susceptible to alternative, clinically feasible drugs, the test should be repeated. This category implies possible clinical applicability in body sites where the drug is physiologically concentrated. This category also provides a buffer zone that prevents small uncontrolled technical factors from causing major discrepancies in interpretation. A report of “Resistant” indicates that the antimicrobial is not likely to inhibit growth of the pathogen if the antimicrobial compound reaches the concentrations usually achievable at the infection site; other therapy should be selected.

Quality Control

Standardized susceptibility test procedures require the use of laboratory controls to monitor and ensure the accuracy and precision of the supplies and reagents used in the assay, and the techniques of the individuals performing the test.^1,2,3Standard oxacillin powder should provide the following range of MIC values 1 noted in Table 2. For the diffusion technique using the 30 mcg cefoxitin disk, the criteria in Table 2 should be achieved.

Table 2. Acceptable Quality Control Ranges for Susceptibility Testing*

Quality Control; Organism | Minimum Inhibitory Concentration; (mcg/mL) | Disk Diffusion Zone Diameters (mm)
Enterococcus faecalis; ATCC ®29212 | 8-32 | -
Staphylococcus aureus; ATCC®25923 | - | 18-24
Staphylococcus aureus; ATCC®29213 | 0.12 - 0.5 | -
Streptococcus pneumonia; ATCC®49619a | - | ≤12b

ATCC=American Type Culture Collection

aDespite the lack of reliable disk diffusion interpretive criteria for S.pneumoniaewith certain beta-lactams, Streptococcus pneumoniaATCC®49619 is the strain designated for QC of all disk diffusion tests with Streptococcus spp.

bDeterioration of oxacillin disk content is best assessed with QC organisms S.aureusATCC®25923, with an acceptable zone diameter for 18-24.

INDICATIONS AND USAGE

Oxacillin is indicated in the treatment of infections caused by penicillinase producing staphylococci which have demonstrated susceptibility to the drug. Cultures and susceptibility tests should be performed initially to determine the causative organism and its susceptibility to the drug (See CLINICAL PHARMACOLOGY– Susceptibility Test Methods).

Oxacillin may be used to initiate therapy in suspected cases of resistant staphylococcal infections prior to the availability of susceptibility test results. Oxacillin should not be used in infections caused by organisms susceptible to penicillin G. If the susceptibility tests indicate that the infection is due to an organism other than a resistant Staphylococcus, therapy should not be continued with oxacillin.

To reduce the development of drug-resistant bacteria and maintain the effectiveness of Oxacillin for Injection, USP and other antibacterial drugs, Oxacillin for Injection, USP should be used only to treat or prevent infections that are proven or strongly suspected to be caused by susceptible bacteria. When culture and susceptibility information are available, they should be considered in selecting or modifying antibacterial therapy. In the absence of such data, local epidemiology and susceptibility patterns may contribute to the empiric selection of therapy.

CONTRAINDICATIONS

A history of a hypersensitivity (anaphylactic) reaction to any penicillin is a contraindication.

WARNINGS

Serious and occasionally fatal hypersensitivity (anaphylactic shock with collapse) reactions have occurred in patients receiving penicillin. The incidence of anaphylactic shock in all penicillin-treated patients is between 0.015 and 0.04 percent. Anaphylactic shock resulting in death has occurred in approximately 0.002 percent of the patients treated.

When oxacillin therapy is indicated, it should be initiated only after a comprehensive patient drug and allergy history has been obtained. If an allergic reaction occurs, oxacillin should be discontinued and appropriate therapy instituted.

Clostridium difficileassociated diarrhea (CDAD) has been reported with use of nearly all antibacterial agents, including oxacillin for injection, USP, and may range in severity from mild diarrhea to fatal colitis. Treatment with antibacterial agents alters the normal flora of the colon leading to overgrowth of C. difficile.

C. difficileproduces toxins A and B which contribute to the development of CDAD. Hypertoxin producing strains of C. difficilecause increased morbidity and mortality, as these infections can be refractory to antimicrobial therapy and may require colectomy. CDAD must be considered in all patients who present with diarrhea following antibiotic use. Careful medical history is necessary since CDAD has been reported to occur over two months after the administration of antibacterial agents.

If CDAD is suspected or confirmed, ongoing antibiotic use not directed against C. difficilemay need to be discontinued. Appropriate fluid and electrolyte management, protein supplementation, antibiotic treatment of C. difficile,and surgical evaluation should be instituted as clinically indicated.

PRECAUTIONS

Oxacillin should generally not be administered to patients with a history of sensitivity to any penicillin. Penicillin should be used with caution in individuals with histories of significant allergies and/or asthma. Whenever allergic reactions occur, penicillin should be withdrawn unless, in the opinion of the physician, the condition being treated is life-threatening and amenable only to penicillin therapy. The use of antibiotics may result in overgrowth of nonsusceptible organisms. If new infections due to bacteria or fungi occur, the drug should be discontinued and appropriate measures taken.

Prescribing Oxacillin for Injection, USP in the absence of a proven or strongly suspected bacterial infection or a prophylactic indication is unlikely to provide benefit to the patient and increases the risk of the development of drug-resistant bacteria.

Laboratory Tests

Bacteriologic studies to determine the causative organisms and their susceptibility to oxacillin should be performed (See CLINICAL PHARMACOLOGY- Microbiology). In the treatment of suspected staphylococcal infections, therapy should be changed to another active agent if culture tests fail to demonstrate the presence of staphylococci.

Periodic assessment of organ system function including renal, hepatic, and hematopoietic should be made during prolonged therapy with oxacillin.

Blood cultures, white blood cell, and differential cell counts should be obtained prior to initiation of therapy and at least weekly during therapy with oxacillin.

Periodic urinalysis, blood urea nitrogen, and creatinine determinations should be performed during therapy with oxacillin and dosage alterations should be considered if these values become elevated. If any impairment of renal function is suspected or known to exist, a reduction in the total dosage should be considered and blood levels monitored to avoid possible neurotoxic reactions.

AST (SGOT) and ALT (SGPT) values should be obtained periodically during therapy to monitor for possible liver function abnormalities.

DRUG INTERACTIONS

Tetracycline, a bacteriostatic antibiotic, may antagonize the bactericidal effect of penicillin and concurrent use of these drugs should be avoided.

Oxacillin blood levels may be increased and prolonged by concurrent administration of probenecid which blocks the renal tubular secretion of penicillins. Probenecid decreases the apparent volume of distribution and slows the rate of excretion by competitively inhibiting renal tubular secretion of penicillins.

Oxacillin-probenecid therapy should be limited to those infections where very high serum levels of oxacillin are necessary.

Carcinogenesis, Mutagenesis, Impairment of Fertility

No long-term animal studies have been conducted with these drugs. Studies on reproduction (nafcillin) in rats and rabbits reveal no fetal or maternal abnormalities before conception and continuously through weaning (one generation).

Pregnancy

Teratogenic Effects

Pregnancy Category B

Reproduction studies performed in the mouse, rat, and rabbit have revealed no evidence of impaired fertility or harm to the fetus due to the penicillinase-resistant penicillins. Human experience with the penicillins during pregnancy has not shown any positive evidence of adverse effects on the fetus. There are, however, no adequate or well-controlled studies in pregnant women showing conclusively that harmful effects of these drugs on the fetus can be excluded. Because animal reproduction studies are not always predictive of human response, this drug should be used during pregnancy only if clearly needed.

Nursing Mothers

Penicillins are excreted in human milk. Caution should be exercised when penicillins are administered to a nursing woman.

Pediatric Use

Because of incompletely developed renal function in pediatric patients, oxacillin may not be completely excreted, with abnormally high blood levels resulting. Frequent blood levels are advisable in this group with dosage adjustments when necessary. All pediatric patients treated with penicillins should be monitored closely for clinical and laboratory evidence of toxic or adverse effects. Safety and effectiveness in pediatric patients have not been established.

Geriatric Use

Clinical studies of oxacillin for injection did not include sufficient number of subjects aged 65 and over to determine whether they respond differently from younger subjects. Other reported clinical experience has not identified differences in responses between the elderly and younger patients. In general, dose selection for an elderly patient should be cautious, usually starting at the low end of the dosing range, reflecting the greater frequency of decreased hepatic, renal, or cardiac function, and of concomitant disease or other drug therapy.

This drug is known to be substantially excreted by the kidney, and the risk of toxic reactions to this drug may be greater in patients with impaired renal function. Because elderly patients are more likely to have decreased renal function, care should be taken in dose selection, and it may be useful to monitor renal function.

Oxacillin for Injection contains 57.4 mg (2.5 mEq) per gram Oxacillin. At the usual recommended doses, patients would receive between 57.4 and 343.8 mg (2.5 and 15 mEq) of sodium. The geriatric population may respond with a blunted natriuresis to salt loading. This may be clinically important with regard to such diseases as congestive heart failure.

Information for Patients

Patients should be counseled that antibacterial drugs including Oxacillin for Injection, USP should only be used to treat bacterial infections. They do not treat viral infections (e.g., the common cold). When Oxacillin for Injection, USP is prescribed to treat a bacterial infection, patients should be told that although it is common to feel better early in the course of therapy, the medication should be taken exactly as directed. Skipping doses or not completing the full course of therapy may: (1) decrease the effectiveness of the immediate treatment, and (2) increase the likelihood that bacteria will develop resistance and will not be treatable by Oxacillin for Injection, USP or other antibacterial drugs in the future.

Diarrhea is a common problem caused by antibiotics which usually ends when the antibiotic is discontinued. Sometimes after starting treatment with antibiotics, patients can develop watery and bloody stools (with or without stomach cramps and fever) even as late as two or more months after having taken the last dose of the antibiotic. If this occurs, patients should contact their physician as soon as possible.

ADVERSE REACTIONS

Body as a Whole

The reported incidence of allergic reactions to penicillin ranges from 0.7 to 10 percent (see WARNINGS). Sensitization is usually the result of treatment but some individuals have had immediate reactions when first treated. In such cases, it is thought that the patients may have had prior exposure to the drug via trace amounts present in milk and vaccines.

Two types of allergic reactions to penicillins are noted clinically, immediate and delayed.

Immediate reactions usually occur within 20 minutes of administration and range in severity from urticaria and pruritus to angioneurotic edema, laryngospasm, bronchospasm, hypotension, vascular collapse and death. Such immediate anaphylactic reactions are very rare (see WARNINGS) and usually occur after parenteral therapy but have occurred in patients receiving oral therapy. Another type of immediate reaction, an accelerated reaction, may occur between 20 minutes and 48 hours after administration and may include urticaria, pruritus, and fever. Although laryngeal edema, laryngospasm, and hypotension occasionally occur, fatality is uncommon.

Delayed allergic reactions to penicillin therapy usually occur after 48 hours and sometimes as late as 2 to 4 weeks after initiation of therapy.

Manifestations of this type of reaction include serum sickness-like symptoms (i.e, fever, malaise, urticaria, myalgia, arthralgia, abdominal pain) and various skin rashes. Nausea, vomiting, diarrhea, stomatitis, black or hairy tongue, and other symptoms of gastrointestinal irritation may occur, especially during oral penicillin therapy.

Nervous System Reactions

Neurotoxic reactions similar to those observed with penicillin G may occur with large intravenous doses of oxacillin, especially with patients with renal insufficiency.

Urogenital Reaction

Renal tubular damage and interstitial nephritis have been associated with the administration of oxacillin. Manifestations of this reaction may include rash, fever, eosinophilia, hematuria, proteinuria, and renal insufficiency. Nephropathy induced by pencillins does not appear to be dose-related and is generally reversible upon prompt discontinuation of therapy.

Gastrointestinal Reaction

Pseudomembranous colitis has been reported with the use of oxacillin. The onset of pseudomembranous colitis symptoms may occur during or after antibiotic treatment (see WARNINGS) .

Metabolic Reactions

Agranulocytosis, neutropenia, and bone marrow depression have been associated with the use of oxacillin. Hepatotoxicity, characterized by fever, nausea, and vomiting associated with abnormal liver function tests, mainly elevated SGOT levels, has been associated with the use of oxacillin.

To report SUSPECTED ADVERSE REACTIONS, contact Onesource at 1-888-217-8103 or FDA at 1-800-FDA-1088 or www.fda.gov/medwatch.

OVERDOSAGE

The signs and symptoms of oxacillin overdosage are those described in the ADVERSE REACTIONSsection. If signs or symptoms occur, discontinue use of the medication, treat symptomatically, and institute appropriate supportive measures.

DOSAGE AND ADMINISTRATION

Bacteriologic studies to determine the causative organisms and their susceptibility to oxacillin should always be performed. Duration of therapy varies with the type of severity of infection as well as the overall condition of the patient; therefore, it should be determined by the clinical and bacteriological response of the patient. In severe staphylococcal infections, therapy with oxacillin should be continued for at least 14 days. Therapy should be continued for at least 48 hours after the patient has become afebrile, asymptomatic, and cultures are negative. Treatment of endocarditis and osteomyelitis may require a longer duration of therapy.

With intravenous administration, particularly in elderly patients, care should be taken because of the possibility of thrombophlebitis.

RECOMMENDED DOSAGES FOR OXACILLIN FOR INJECTION, USP

Drug | Adults | Infants and Children < 40 kg (88 lbs) | Other Recommendations
Oxacillin | 250 to 500 mg IM or IV every 4 to 6 hours (mild to moderate infections) | 50 mg/kg/day IM or IV in equally divided doses every 6 hours (mild to moderate infections)
Oxacillin | 1 gram IM or IV every 4 to 6 hours (severe infections) | 100 mg/kg/day IM or IV in equally divided doses every 4 to 6 hours (severe infections) | Premature and Neonates 25 mg/kg/day IM or IV

For Intramuscular Use:Use Sterile Water for Injection, USP. Add 5.7 mL to the 1 gram vial and 11.5 mL to the 2 gram vial. Shake well until a clear solution is obtained. After reconstitution, vials will contain 250 mg of active drug per 1.5 mL of solution. The reconstituted solution is stable for 3 days at 70°F or for one week under refrigeration (40° F)

For Direct Intravenous Use:Use Sterile Water for Injection, USP or Sodium Chloride Injection, USP. Add 10 mL to the 1 gram vial and 20 mL to the 2 gram vial. Withdraw the entire contents and administer slowly over a period of approximately10 minutes.

For Administration by Intravenous Drip:Reconstitute as directed above (For Direct Intravenous Use) prior to diluting with Intravenous Solution.

STABILITY PERIODS FOR OXACILLIN FOR INJECTION, USP

Concentration mg/mL | Sterile water for Injection | 0.9% sodium chloride Injection, USP | M/6 Molar Sodium Lactate Solution | 5% Dextrose in water | 5% Dextrose in 0.45% sodium chloride | 10% Invert Sugar Injection, USP | Lactated Ringers Solution
 | ROOM TEMPERATURE (25° C)
10 to100 | 4 Days | 4 Days
10 to 30 |  |  | 24 Hrs |  | 24 Hrs
0.5 to 2 |  |  |  | 6 Hrs |  | 6 Hrs | 6 Hrs
 | REFRIGERATION (4° C)
10 to 100 | 7 Days | 7 Days
10 to 30 |  |  | 4 Days | 4 Days | 4 Days | 4 days | 4 Days
 | FROZEN (-15° C)
50 to 100 | 30 Days
250/1.5 mL | 30 Days
100 |  | 30 Days
10 to 100 |  |  | 30 Days | 30 Days | 30 Days | 30 Days | 30 Days

Stability studies on oxacillin sodium at concentrations of 0.5 mg/mL and 2 mg/mL in various intravenous solutions listed below indicate the drug will lose less than 10% activity at room temperature (70°F) during a 6-hour period.

IV Solution

5% Dextrose in Normal Saline

10% D-Fructose in Water

10% D-Fructose in Normal Saline

Lactated Potassic Saline Injection

10% Invert Sugar in Normal Saline

10% Invert Sugar Plus 0.3% Potassium Chloride in Water

Travert 10% Electrolyte #1

Travert 10% Electrolyte #2

Travert 10% Electrolyte #3

Only those solutions listed above should be used for the intravenous infusion of oxacillin sodium. The concentration of the antibiotic should fall within the range specified. The drug concentration and the rate and volume of the infusion should be adjusted so that the total dose of oxacillin is administered before the drug loses its stability in the solution in use.

If another agent is used in conjunction with oxacillin therapy, it should not be physically mixedwith oxacillin but should be administered separately.

Parenteral drug products should be inspected visually for particulate matter and discoloration prior to administration whenever solution and container permit.

Do not add supplementary medication to oxacillin for injection, USP.

HOW SUPPLIED

Each vial of Oxacillin for Injection, USP contains oxacillin sodium monohydrate equivalent to 1 gram or 2 grams of oxacillin and is available as:

NDC | Oxacillin for Injection, USP | Package factor
83270-306-10 | 1 gram vial* | 10s
83270-307-10 | 2 gram vial* | 10s

* Vial stoppers are not made with natural rubber latex.

Store the dry powder at 20^0to 25^0C (68^0to 77^0F) [See USP Controlled Room Temperature].

REFERENCES

1. Clinical and Laboratory Standards Institute (CLSI). Methods for Dilution Antimicrobial Susceptibility Tests for Bacteria That Grow Aerobically; Approved Standard-Tenth Edition. CLSI Document M07-A10. Clinical and Laboratory Standards Institute, 950 West Valley Road, Suite 2500, Wayne, Pennsylvania 19087, USA, 2015.

2. Clinical and Laboratory Standards Institute (CLSI). Performance Standards for Antimicrobial Susceptibility Testing;Twenty-fifth Informational Supplement. CLSI Document M100-S25. Clinical and Laboratory Standards Institute, 950 West Valley Road, Suite 2500, Wayne, Pennsylvania 19087, USA-2015.

3. Clinical and Laboratory Standards Institute (CLSI). Performance Standards for Antimicrobial Disk Susceptibility Tests; Approved Standard Twelfth Edition.CLSI Document M02-A112. Clinical and Laboratory Standards Institute, 950 West Valley Road, Suite 2500, Wayne, Pennsylvania 19087, USA, 2015.

Manufactured by:

Onesource Specialty Pharma Limited

Beta Lactam Division,
Bangalore India.

Rev. 12/2025

Package/Label Display Panel

vial label 1g

carton label 1g

vial label 2g

carton label 2g